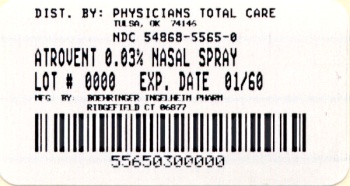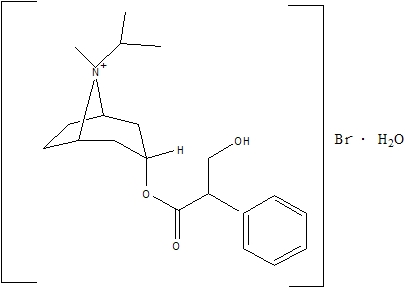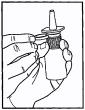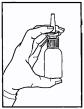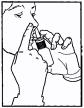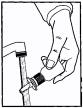 DRUG LABEL: Atrovent
NDC: 54868-5565 | Form: SPRAY, METERED
Manufacturer: Physicians Total Care, Inc.
Category: prescription | Type: HUMAN PRESCRIPTION DRUG LABEL
Date: 20100910

ACTIVE INGREDIENTS: IPRATROPIUM BROMIDE 21 ug/1 1
INACTIVE INGREDIENTS: BENZALKONIUM CHLORIDE; EDETATE DISODIUM; SODIUM CHLORIDE; SODIUM HYDROXIDE; HYDROCHLORIC ACID; WATER

Atrovent®
(ipratropium bromide)
Nasal Spray
0.03%
21mcg/spray

ATTENTION PHARMACIST: Detach “Patient's Instructions for Use” from package insert and dispense with the product.

Prescribing Information

DESCRIPTION

The active ingredient in ATROVENT Nasal Spray is ipratropium bromide (as the monohydrate). It is an anticholinergic agent chemically described as 8-azoniabicyclo[3.2.1]octane, 3-(3-hydroxy-1-oxo-2-phenylpropoxy)-8-methyl-8-(1-methylethyl)-, bromide monohydrate, (3-endo, 8-syn)-: a synthetic quaternary ammonium compound, chemically related to atropine. The structural formula is:

C20H30BrNO3•H2O ipratropium bromide Mol. Wt. 430.4

Ipratropium bromide is a white to off-white crystalline substance, freely soluble in water and methanol, sparingly soluble in ethanol, and insoluble in non-polar media. In aqueous solution, it exists in an ionized state as a quaternary ammonium compound.

ATROVENT Nasal Spray 0.03% is a metered-dose, manual pump spray unit which delivers 21 mcg ipratropium bromide (on an anhydrous basis) per spray (70 μL) in an isotonic aqueous solution, pH-adjusted to 4.7 with hydrochloric acid and/or sodium hydroxide (if needed). It also contains benzalkonium chloride, edetate disodium, sodium chloride, and purified water. Each bottle contains 345 sprays.

CLINICAL PHARMACOLOGY

Mechanism of Action

Ipratropium bromide is an anticholinergic (parasympatholytic) agent which, based on animal studies, appears to inhibit vagally-mediated reflexes by antagonizing the action of acetylcholine, the transmitter agent released at the neuromuscular junctions in the lung. In humans, ipratropium bromide has anti-secretory properties and, when applied locally, inhibits secretions from the serous and seromucous glands lining the nasal mucosa. Ipratropium bromide is a quaternary amine that minimally crosses the nasal and gastrointestinal membranes and the blood-brain barrier, resulting in a reduction of the systemic anticholinergic effects (e.g., neurologic, ophthalmic, cardiovascular, and gastrointestinal effects) that are seen with tertiary anticholinergic amines.

Pharmacokinetics

Absorption: Ipratropium bromide is poorly absorbed into the systemic circulation following oral administration (2-3%). Less than 20% of an 84 mcg per nostril dose was absorbed from the nasal mucosa of normal volunteers, induced-cold patients, or perennial rhinitis patients.

Distribution: Ipratropium bromide is minimally bound (0 to 9% in vitro) to plasma albumin and α1-acid glycoprotein. Its blood/plasma concentration ratio was estimated to be about 0.89. Studies in rats have shown that ipratropium bromide does not penetrate the blood-brain barrier.

Metabolism: Ipratropium bromide is partially metabolized to ester hydrolysis products, tropic acid and tropane. These metabolites appear to be inactive based on in vitro receptor affinity studies using rat brain tissue homogenates.

Elimination: After intravenous administration of 2 mg ipratropium bromide to 10 healthy volunteers, the terminal half-life of ipratropium was approximately 1.6 hours. The total body clearance and renal clearance were estimated to be 2,505 and 1,019 mL/min, respectively. The amount of the total dose excreted unchanged in the urine (Ae) within 24 hours was approximately one-half of the administered dose.

Pediatrics: Following administration of 42 mcg of ipratropium bromide per nostril two or three times a day in perennial rhinitis patients 6-18 years old, the mean amounts of the total dose excreted unchanged in the urine (8.6 to 11.1%) were higher than those reported in adult volunteers or adult perennial rhinitis patients (3.7 to 5.6%). Plasma ipratropium concentrations were relatively low (ranging from undetectable up to 0.49 ng/mL). No correlation of the amount of the total dose excreted unchanged in the urine (Ae) with age or gender was observed in the pediatric population.

Special Populations: Gender does not appear to influence the absorption or excretion of nasally administered ipratropium bromide. The pharmacokinetics of ipratropium bromide have not been studied in patients with hepatic or renal insufficiency or in the elderly.

Drug-Drug Interactions: No specific pharmacokinetic studies were conducted to evaluate potential drug-drug interactions.

Pharmacodynamics

In two single-dose trials (n=17), doses up to 336 mcg of ipratropium bromide did not significantly affect pupillary diameter, heart rate, or systolic/diastolic blood pressure. Similarly, in patients with induced-colds, Atrovent® (ipratropium bromide) Nasal Spray 0.06% (84 mcg/nostril four times a day), had no significant effects on pupillary diameter, heart rate or systolic/diastolic blood pressure.

Two nasal provocation trials in perennial rhinitis patients (n=44) using ipratropium bromide nasal spray showed a dose dependent increase in inhibition of methacholine induced nasal secretion with an onset of action within 15 minutes (time of first observation).

Controlled clinical trials demonstrated that intranasal fluorocarbon-propelled ipratropium bromide does not alter physiologic nasal functions (e.g., sense of smell, ciliary beat frequency, mucociliary clearance, or the air conditioning capacity of the nose).

Clinical Trials

The clinical trials for Atrovent® (ipratropium bromide) Nasal Spray 0.03% were conducted in patients with nonallergic perennial rhinitis (NAPR) and in patients with allergic perennial rhinitis (APR). APR patients were those who experienced symptoms of nasal hypersecretion and nasal congestion or sneezing when exposed to specific perennial allergens (e.g., dust mites, molds) and were skin test positive to these allergens. NAPR patients were those who experienced symptoms of nasal hypersecretion and nasal congestion or sneezing throughout the year, but were skin test negative to common perennial allergens.

In four controlled, four- and eight-week comparisons of ATROVENT Nasal Spray 0.03% (42 mcg per nostril, two or three times daily) with its vehicle, in patients with allergic or nonallergic perennial rhinitis, there was a statistically significant decrease in the severity and duration of rhinorrhea in the ATROVENT group throughout the entire study period. An effect was seen as early as the first day of therapy.

There was no effect of ATROVENT Nasal Spray 0.03% on degree of nasal congestion, sneezing, or postnasal drip. The response to ATROVENT Nasal Spray 0.03% did not appear to be affected by the type of perennial rhinitis (NAPR or APR), age, or gender. No controlled clinical trials directly compared the efficacy of BID versus TID treatment.

INDICATIONS AND USAGE

ATROVENT Nasal Spray 0.03% is indicated for the symptomatic relief of rhinorrhea associated with allergic and nonallergic perennial rhinitis in adults and children age 6 years and older. ATROVENT Nasal Spray 0.03% does not relieve nasal congestion, sneezing, or postnasal drip associated with allergic or nonallergic perennial rhinitis.

CONTRAINDICATIONS

Atrovent® (ipratropium bromide) Nasal Spray 0.03% is contraindicated in patients with a history of hypersensitivity to atropine or its derivatives, or to any of the other ingredients.

WARNINGS

Immediate hypersensitivity reactions may occur after administration of ipratropium bromide, as demonstrated by urticaria, angioedema, rash, bronchospasm, anaphylaxis, and oropharyngeal edema. If such a reaction occurs, therapy with ATROVENT Nasal Spray 0.03% should be stopped at once and alternative treatment should be considered.

PRECAUTIONS

General

1. Effects Seen with Anticholinergic Drugs: ATROVENT Nasal Spray 0.03% should be used with caution in patients with narrow-angle glaucoma, prostatic hyperplasia, or bladder neck obstruction, particularly if they are receiving an anticholinergic by another route.

2. Use in Hepatic or Renal Disease: ATROVENT Nasal Spray 0.03% has not been studied in patients with hepatic or renal insufficiency. It should be used with caution in those patient populations.

Information for Patients

Patients should be advised that temporary blurring of vision, precipitation or worsening of narrow-angle glaucoma, mydriasis, increased intraocular pressure, acute eye pain or discomfort, visual halos or colored images in association with red eyes from conjunctival and corneal congestion may result if ATROVENT Nasal Spray 0.03% comes into direct contact with the eyes. Patients should be instructed to avoid spraying ATROVENT Nasal Spray 0.03% in or around their eyes. Patients who experience eye pain, blurred vision, excessive nasal dryness, or episodes of nasal bleeding should be instructed to contact their doctor. To ensure proper dosing, patients should be advised not to alter the size of the nasal spray opening. Patients should be reminded to carefully read and follow the accompanying Patient's Instructions for Use.

Since dizziness, accommodation disorder, mydriasis, and blurred vision may occur with use of ATROVENT, patients should be cautioned about engaging in activities requiring balance and visual acuity such as driving a car or operating appliances, machinery, etc.

Drug Interactions

No controlled clinical trials were conducted to investigate potential drug-drug interactions. There is potential for an additive interaction with other concomitantly administered medications with anticholinergic properties, including ATROVENT for oral inhalation.

Carcinogenesis, Mutagenesis, Impairment of Fertility

Two-year oral carcinogenicity studies in rats and mice have revealed no carcinogenic activity at doses up to 6 mg/kg. This dose corresponds in rats and mice to approximately 190 and 95 times the maximum recommended daily intranasal dose in adults, respectively, and approximately 110 and 55 times the maximum recommended daily intranasal dose in children, respectively, on a mg/m^2 basis. Results of various mutagenicity studies (Ames test, mouse dominant lethal test, mouse micronucleus test, and chromosome aberration of bone marrow in Chinese hamsters) were negative.

Fertility of male or female rats at oral doses up to 50 mg/kg (approximately 1,600 times the maximum recommended daily intranasal dose in adults on a mg/m^2 basis) was unaffected by ipratropium bromide administration. At an oral dose of 500 mg/kg (approximately 16,000 times the maximum recommended daily intranasal dose in adults on a mg/m^2 basis), ipratropium bromide produced a decrease in the conception rate.

Pregnancy

Teratogenic Effects: Pregnancy Category B.

Oral reproduction studies were performed at doses of 10 mg/kg in mice, 1000 mg/kg in rats and 125 mg/kg in rabbits. These doses correspond, in each species, respectively, to approximately 160, 32,000, and 8,000 times the maximum recommended daily intranasal dose in adults on a mg/m^2 basis. Inhalation reproduction studies were conducted in rats and rabbits at doses of 1.5 and 1.8 mg/kg, respectively, (approximately 50 and 120 times, respectively, the maximum recommended daily intranasal dose in adults on a mg/m^2 basis). These studies demonstrated no evidence of teratogenic effects as a result of ipratropium bromide. At oral doses 90 mg/kg and above in rats (approximately 2,900 times the maximum recommended daily intranasal dose in adults on a mg/m^2 basis) embryotoxicity was observed as increased resorption. This effect is not considered relevant to human use due to the large doses at which it was observed and the difference in route of administration. However, no adequate or well controlled studies have been conducted in pregnant women. Because animal reproduction studies are not always predictive of human response, Atrovent® (ipratropium bromide) Nasal Spray 0.03% should be used during pregnancy only if clearly needed.

Nursing Mothers

It is known that some ipratropium bromide is systemically absorbed following nasal administration; however the portion which may be excreted in human milk is unknown. Because lipid-insoluble quaternary cations pass into breast milk, caution should be exercised when ATROVENT Nasal Spray 0.03% is administered to a nursing mother.

Pediatric Use

The safety of Atrovent® (ipratropium bromide) Nasal Spray 0.03% at a dose of two sprays (42 mcg) per nostril two or three times daily (total dose 168 to 252 mcg/day) has been demonstrated in 77 pediatric patients 6-12 years of age in placebo-controlled, 4-week trials and in 55 pediatric patients in active-controlled, 6 month trials. The effectiveness of ATROVENT Nasal Spray 0.03% for the treatment of rhinorrhea associated with allergic and nonallergic perennial rhinitis in this pediatric age group is based on an extrapolation of the demonstrated efficacy of ATROVENT Nasal Spray 0.03% in adults with these conditions and the likelihood that the disease course, pathophysiology, and the drug's effects are substantially similar to that of the adults. The recommended dose for the pediatric population is based on within and cross-study comparisons of the efficacy of ATROVENT Nasal Spray 0.03% in adults and pediatric patients and on its safety profile in both adults and pediatric patients. The safety and effectiveness of ATROVENT Nasal Spray 0.03% in patients under 6 years of age have not been established.

ADVERSE REACTIONS

Adverse reaction information on ATROVENT Nasal Spray 0.03% in patients with perennial rhinitis was derived from four multicenter, vehicle-controlled clinical trials involving 703 patients (356 patients on ATROVENT and 347 patients on vehicle), and a one-year, open-label, follow-up trial. In three of the trials, patients received ATROVENT Nasal Spray 0.03% three times daily, for eight weeks. In the other trial, ATROVENT Nasal Spray 0.03% was given to patients two times daily for four weeks. Of the 285 patients who entered the open-label, follow-up trial, 232 were treated for 3 months, 200 for 6 months, and 159 up to one year. The majority (>86%) of patients treated for one year were maintained on 42 mcg per nostril, two or three times daily, of ATROVENT Nasal Spray 0.03%.

Table 1 shows adverse events, and the frequency that these adverse events led to the discontinuation of treatment, reported for patients who received ATROVENT Nasal Spray 0.03% at the recommended dose of 42 mcg per nostril, or vehicle two or three times daily for four or eight weeks. Only adverse events reported with an incidence of at least 2.0% in the ATROVENT group and higher in the ATROVENT group than in the vehicle group are shown.

Table 1 % of Patients Reporting Events^+
 | Atrovent® (ipratropium bromide) |  | Vehicle Control
 | Nasal Spray 0.03%
 | (n=356) |  | (n=347)
 | Incidence % | Discontinued % | Incidence % | Discontinued %
Headache | 9.8 | 0.6 | 9.2 | 0.0
Upper respiratory
tract infection | 9.8 | 1.4 | 7.2 | 1.4
Epistaxis^1 | 9.0 | 0.3 | 4.6 | 0.3
Rhinitis*
Nasal dryness | 5.1 | 0.0 | 0.9 | 0.3
Nasal irritation^2 | 2.0 | 0.0 | 1.7 | 0.6
Other nasal symptoms^3 | 3.1 | 1.1 | 1.7 | 0.3
Pharyngitis | 8.1 | 0.3 | 4.6 | 0.0
Nausea | 2.2 | 0.3 | 0.9 | 0.0
^+ This table includes adverse events which occurred at an incidence rate of at least 2.0% in the ATROVENT group and more frequently in the ATROVENT group than in the vehicle group.
^1 Epistaxis reported by 7.0% of ATROVENT patients and 2.3% of vehicle patients, blood-tinged mucus by 2.0% of ATROVENT patients and 2.3% of vehicle patients.
^2 Nasal irritation includes reports of nasal itching, nasal burning, nasal irritation, and ulcerative rhinitis.
^3 Other nasal symptoms include reports of nasal congestion, increased rhinorrhea, increased rhinitis, posterior nasal drip, sneezing, nasal polyps, and nasal edema.
* All events are listed by their WHO term; rhinitis has been presented by descriptive terms for clarification.

ATROVENT Nasal Spray 0.03% was well tolerated by most patients. The most frequently reported nasal adverse events were transient episodes of nasal dryness or epistaxis. These adverse events were mild or moderate in nature, none was considered serious, none resulted in hospitalization and most resolved spontaneously or following a dose reduction. Treatment for nasal dryness and epistaxis was required infrequently (2% or less) and consisted of local application of pressure or a moisturizing agent (e.g., petroleum jelly or saline nasal spray). Patient discontinuation for epistaxis or nasal dryness was infrequent in both the controlled (0.3% or less) and one-year, open-label (2% or less) trials. There was no evidence of nasal rebound (i.e., a clinically significant increase in rhinorrhea, posterior nasal drip, sneezing or nasal congestion severity compared to baseline) upon discontinuation of double-blind therapy in these trials.

Adverse events reported by less than 2% of the patients receiving ATROVENT Nasal Spray 0.03% during the controlled clinical trials or during the open-label follow-up trial, which are potentially related to ATROVENT’s local effects or systemic anticholinergic effects include: dry mouth/throat, dizziness, ocular irritation, blurred vision, conjunctivitis, hoarseness, cough, and taste perversion.

There were infrequent reports of skin rash in both the controlled and uncontrolled clinical studies.

Post-Marketing Experience

Allergic-type reactions such as skin rash, angioedema, including that of the throat, tongue, lips and face, generalized urticaria (including giant urticaria), laryngospasm, and anaphylactic reactions have been reported with Atrovent® (ipratropium bromide) Nasal Spray 0.03% and for other ipratropium bromide-containing products, with positive rechallenge in some cases.

Additional side effects identified from the published literature and/or post-marketing surveillance on the use of ipratropium bromide-containing products (singly or in combination with albuterol), include: urinary retention, prostatic disorders, mydriasis, cases of precipitation or worsening of narrow-angle glaucoma, acute eye pain, wheezing, dryness of the oropharynx, sinusitis, tachycardia, palpitations, pain, edema, gastrointestinal distress (diarrhea, nausea, vomiting), bowel obstruction, constipation, nasal discomfort, throat irritation, hypersensitivity, accommodation disorder, intraocular pressure increased, glaucoma, halo vision, conjunctival hyperaemia, corneal edema, heart rate increased, bronchospasm, pharyngeal edema, gastrointestinal motility disorder, mouth edema, stomatitis, and pruritus.

After oral inhalation of ipratropium bromide in patients suffering from COPD/Asthma supraventricular tachycardia and atrial fibrillation have been reported.

OVERDOSAGE

Acute overdosage by intranasal administration is unlikely since ipratropium bromide is not well absorbed systemically after intranasal or oral administration. Following administration of a 20 mg oral dose (equivalent to ingesting more than four bottles of ATROVENT Nasal Spray 0.03%) to 10 male volunteers, no change in heart rate or blood pressure was noted. Following a 2 mg intravenous infusion over 15 minutes to the same 10 male volunteers, plasma ipratropium concentrations of 22-45 ng/mL were observed (>100 times the concentrations observed following intranasal administration). Following intravenous infusion these 10 volunteers had a mean increase of heart rate of 50 bpm and less than 20 mmHg change in systolic or diastolic blood pressure at the time of peak ipratropium levels.

Oral median lethal doses of ipratropium bromide were greater than 1,001 mg/kg in mice (approximately 16,000 and 9,500 times the maximum recommended daily intranasal dose in adults and children, respectively, on a mg/m^2 basis), 1,663 mg/kg in rats (approximately 53,000 and 32,000 times the maximum recommended daily intranasal dose in adults and children, respectively, on a mg/m^2 basis), and 400 mg/kg in dogs (approximately 43,000 and 25,000 times the maximum recommended daily intranasal dose in adults and children, respectively, on a mg/m^2 basis).

DOSAGE AND ADMINISTRATION

The recommended dose of ATROVENT Nasal Spray 0.03% is two sprays (42 mcg) per nostril two or three times daily (total dose 168 to 252 mcg/day) for the symptomatic relief of rhinorrhea associated with allergic and nonallergic perennial rhinitis in adults and children age 6 years and older. Optimum dosage varies with the response of the individual patient.

Initial pump priming requires seven sprays of the pump. If used regularly as recommended, no further priming is required. If not used for more than 24 hours, the pump will require two sprays, or if not used for more than seven days, the pump will require seven sprays to reprime. Avoid spraying into eyes.

HOW SUPPLIED

Atrovent® (ipratropium bromide) Nasal Spray 0.03% is supplied in a white high density polyethylene (HDPE) bottle fitted with a metered nasal spray pump, a green safety clip to prevent accidental discharge of the spray, and a clear plastic dust cap. It contains 31.1g of product formulation, 345 sprays, each delivering 21 mcg of ipratropium bromide per spray (70 μL), or 28 days of therapy at the maximum recommended dose (two sprays per nostril three times a day) (NDC 54868-5565-0).

STORAGE AND HANDLING

Store tightly closed at 25°C (77°F); excursions permitted to 15°-30°C (59°-86°F) [see USP Controlled Room Temperature]. Avoid freezing. Keep out of reach of children. Do not spray in the eyes.

Address medical inquiries to: http://us.boehringer-ingelheim.com, (800) 542-6257 or (800) 459-9906 TTY.

Patients should be reminded to read and follow the accompanying “Patient’s Instructions for Use”, which should be dispensed with the product.

Distributed by:
Boehringer Ingelheim Pharmaceuticals, Inc.
Ridgefield, CT 06877 USA

Licensed from:
Boehringer Ingelheim International GmbH

Copyright 2010 Boehringer Ingelheim International GmbH
ALL RIGHTS RESERVED

Rev: July 2010

IT4000DG1710
10001900/06

Relabeling of "Additional Barcode Label" by:
Physicians Total Care, Inc.
Tulsa, OK 74146

Patient's Instructions for Use

Atrovent®
(ipratropium bromide)
Nasal Spray 0.03%

21 mcg/spray

Read complete instructions carefully before using.

In order to ensure proper dosing, do not attempt to change the size of the spray opening.

ATROVENT Nasal Spray 0.03% is indicated for the symptomatic relief of rhinorrhea (runny nose) associated with allergic and nonallergic perennial rhinitis in adults and children age 6 years and older. ATROVENT Nasal Spray 0.03% does not relieve nasal congestion, sneezing, or postnasal drip associated with allergic or nonallergic perennial rhinitis.

Read complete instructions carefully and use only as directed.

To Use:

1. Remove the clear plastic dust cap and the green safety clip from the nasal spray pump (Figure 1). The safety clip prevents the accidental discharge of the spray in your pocket or purse.
  Figure 1
2. The nasal spray pump must be primed before Atrovent® (ipratropium bromide) Nasal Spray 0.03% is used for the first time. To prime the pump, hold the bottle with your thumb at the base and your index and middle fingers on the white shoulder area. Make sure the bottle points upright and away from your eyes. Press your thumb firmly and quickly against the bottle seven times (Figure 2). The pump is now primed and can be used. Your pump should not have to be reprimed unless you have not used the medication for more than 24 hours; repriming the pump will only require two sprays. If you have not used your nasal spray for more than seven days, repriming the pump will require seven sprays.
  Figure 2
3. Before using ATROVENT Nasal Spray 0.03%, blow your nose gently to clear your nostrils if necessary.
4. Close one nostril by gently placing your finger against the side of your nose, tilt your head slightly forward and, keeping the bottle upright, insert the nasal tip into the other nostril (Figure 3). Point the tip toward the back and outer side of the nose.
  Figure 3
5. Press firmly and quickly upwards with the thumb at the base while holding the white shoulder portion of the pump between your index and middle fingers. Following each spray, sniff deeply and breathe out through your mouth.
6. After spraying the nostril and removing the unit, tilt your head backwards for a few seconds to let the spray spread over the back of the nose.
7. Repeat steps 4 through 6 in the same nostril.
8. Repeat steps 4 through 7 in the other nostril (i.e., two sprays per nostril).
9. Replace the clear plastic dust cap and safety clip.
10. At some time before the medication is completely used up, you should consult your physician or pharmacist to determine whether a refill is needed. You should not take extra doses or stop using Atrovent® (ipratropium bromide) Nasal Spray 0.03% without consulting your physician.

To Clean:

If the nasal tip becomes clogged, remove the clear plastic dust cap and safety clip. Hold the nasal tip under running, warm tap water (Figure 4) for about a minute. Dry the nasal tip, reprime the nasal spray pump (step 2 above), and replace the plastic dust cap and safety clip.

Figure 4

Caution:

ATROVENT Nasal Spray 0.03% is intended to relieve your rhinorrhea (runny nose) with regular use. It is therefore important that you use ATROVENT Nasal Spray 0.03% as prescribed by your physician. For most patients, some improvement in runny nose is usually apparent during the first full day of treatment with ATROVENT Nasal Spray 0.03%. Some patients may require up to two weeks of treatment to obtain maximum benefit.

Do not spray ATROVENT Nasal Spray 0.03% in your eyes. Should this occur, immediately flush your eye with cool tap water for several minutes. If you accidentally spray ATROVENT Nasal Spray 0.03% in your eyes, you may experience a temporary blurring of vision, visual halos or colored images in association with red eyes from conjunctival and corneal congestion, development or worsening of narrow-angle glaucoma, pupil dilation, or acute eye pain/discomfort, and increased sensitivity to light, which may last a few hours. Should acute eye pain or blurred vision occur, contact your doctor.

Should you experience excessive nasal dryness or episodes of nasal bleeding contact your doctor.

If you have glaucoma or difficulty urinating due to an enlargement of the prostate, be sure to tell your physician prior to using ATROVENT Nasal Spray 0.03%.

If you are pregnant or you are breast feeding your baby, be sure to tell your physician prior to using ATROVENT Nasal Spray 0.03%.

Address medical inquiries to: http://us.boehringer-ingelheim.com, (800) 542-6257 or (800) 459-9906 TTY.

Store tightly closed at 25°C (77°F); excursions permitted to 15°-30°C (59°-86°F) [see USP Controlled Room Temperature]. Avoid freezing. Keep out of reach of children.

Distributed by:
Boehringer Ingelheim Pharmaceuticals, Inc.
Ridgefield, CT 06877 USA

Licensed from:
Boehringer Ingelheim International GmbH

Copyright 2010 Boehringer Ingelheim International GmbH
ALL RIGHTS RESERVED

Rev: July 2010

IT4000DG1710
10001900/06

PACKAGE LABEL

Atrovent

Nasal Spray 0.03%

21 mcg/spray

30 mL (345 metered sprays)